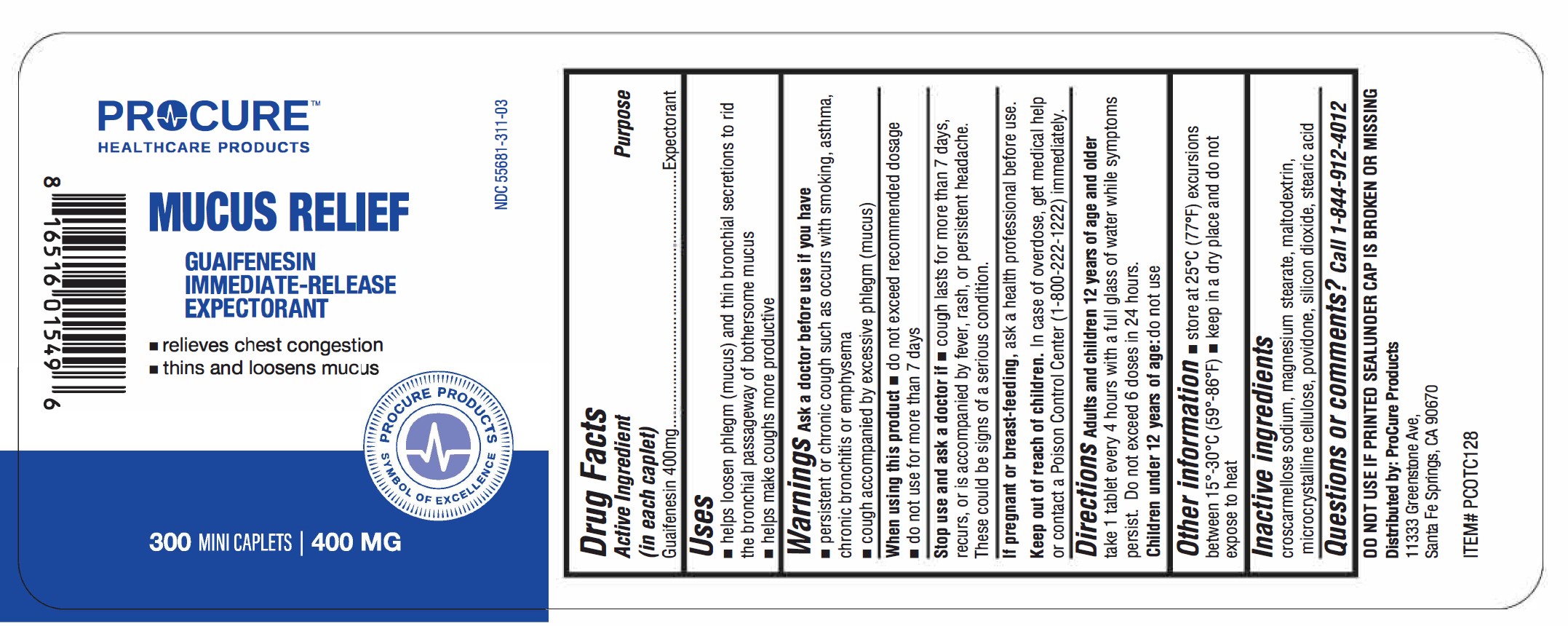 DRUG LABEL: Mucus Relief
NDC: 55681-311 | Form: TABLET
Manufacturer: TWIN MED LLC
Category: otc | Type: HUMAN OTC DRUG LABEL
Date: 20250703

ACTIVE INGREDIENTS: GUAIFENESIN 400 mg/1 1
INACTIVE INGREDIENTS: CROSCARMELLOSE SODIUM; MALTODEXTRIN; SILICON DIOXIDE; MAGNESIUM STEARATE; CELLULOSE, MICROCRYSTALLINE; STEARIC ACID; POVIDONE

Mucus Relief - Guaifenesin 400 mg Caplets

Active ingredient (in each tablet)

Guaifenesin 400 mg

Purpose

Expectorant

Uses

- helps loosen phlegm (mucus) and thin bronchial secretions to rid the bronchial passageway of bothersome mucus
- helps make couohs more productive

Warnings

ask a doctor before use if you have

- persistent or chronic cough such as occurs with smoking, asthma, chronic bronchitis or emphysema
- cough accompanied by excessive phlegm (mucus)

When using this product

- do not exceed recommended dosage
- do not use for more than 7 days

Stop use and ask a doctor if

- cough lasts for more than 7 days, recurs, or is accompanied by fever, rash, or persistent headache.

These could be signs of a serious condition.

PREGNANCY OR BREAST FEEDING

If pregnant or breast-feeding,ask a health professional before use.

Keep out of reach of children.

In case of overdose, get medical help or contact a Poison Control Center (1 ·800-222-1222) immediately.

Directions:

- adults and children 12 years of age and over:take 1 tablet every 4 hours with a full glass of water while symptoms persist. Do not exceed 6 doses in 24 hours.
- children under 12 years:do not use

Other information

- store at 25°C (77°F) excursions between 15°-30°C (59°-86°F)
- keep in a dry place and do not expose to heat

Inactive ingredients

croscarmellose sodium, magnesium stearate, maltodextrin, microcrystalline cellulose, povidone, silicon dioxide, stearic acid

Questions or Comments

Call 1-844-912·4012

Principal Display Panel

DD NDT USE IF PRINTED SEALUNDER CAP IS BRDKEN OR MISSING

Dlsbibuted by: Procure Products
11333 Greenstone Ave,
Santa Fe Springs, CA 90670